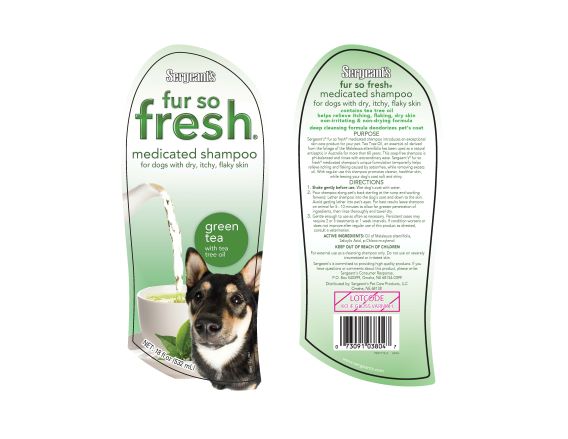 DRUG LABEL: Fur So Fresh
NDC: 21091-804 | Form: SHAMPOO
Manufacturer: Sergeants Pet Care Products LLC
Category: animal | Type: OTC ANIMAL DRUG LABEL
Date: 20240412

ACTIVE INGREDIENTS: TEA TREE OIL 0.46 g/650 g; SALICYLIC ACID 1.62 g/650 g; CHLOROXYLENOL 3.25 g/650 g
INACTIVE INGREDIENTS: Water 377.65 g/650 g; FD&C YELLOW NO. 5 0.003 g/650 g; FD&C BLUE NO. 1 00.00117 g/650 g; DMDM HYDANTOIN 1.95 g/650 g; SODIUM LAURYL SULFATE 32.50 g/650 g; PEG-150 DISTEARATE 9.42 g/650 g; POLYSORBATE 20 5.20 g/650 g; GLYCERYL MONOSTEARATE 19.5 g/650 g; SODIUM C14-16 OLEFIN SULFONATE 143.0 g/650 g; COCAMIDE 29.25 g/650 g; COCAMIDOPROPYL BETAINE 29.25 g/650 g

PURPOSE

Sergeant’s fur so fresh medicated shampoo introduces an exceptional skin care product for your pet. Tea Tree Oil, an essential oil derived
from the foliage of the Malaleuca alternifolia has been used as a natural antiseptic in Australia for more than 60 years. This soap-free shampoo is
pH-balanced and rinses with extraordinary ease. Sergeant’s® fur so fresh® medicated shampoo’s unique formulation temporarily helps
relieve itching and flaking caused by seborrhea, while removing excess oil. With regular use this shampoo promotes cleaner, healthier skin,
while leaving your dog’s coat soft and shiny.

DIRECTIONS

1. Shake gently before use. Wet dog’s coat with water.
2. Pour shampoo along pet’s back starting at the rump and working forward. Lather shampoo into the dog’s coat and down to the skin. Avoid getting lather into pet’s eyes. For best results leave shampoo on animal for 5 - 10 minutes to allow for greater penetration of ingredients, then rinse thoroughly and towel dry.
3. Gentle enough to use as often as necessary. Persistent cases may require 2 or 3 treatments at 1 week intervals. If condition worsens or does not improve after regular use of this product as directed, consult a veterinarian.

ACTIVE INGREDIENTS:

Oil of Malaleuca alternifolia, Salicylic Acid, p-Chloro-m-xylenol.

KEEP OUT OF REACH OF CHILDREN

WARNINGS AND PRECAUTIONS

For external use as a cleansing shampoo only. Do not use on severely traumatized or irritated skin.

PACKAGE LABEL

P007112 RRRC | P007113-2 AOIA